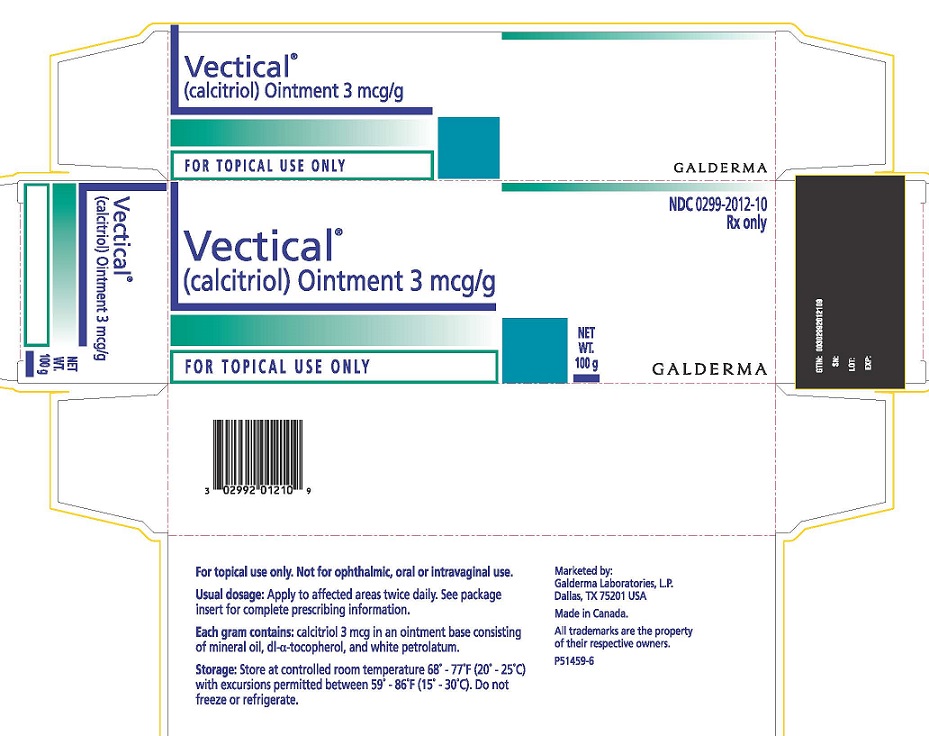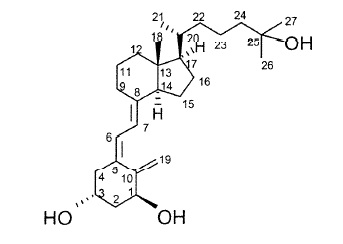 DRUG LABEL: Vectical
NDC: 0299-2012 | Form: OINTMENT
Manufacturer: Galderma Laboratories, L.P.
Category: prescription | Type: HUMAN PRESCRIPTION DRUG LABEL
Date: 20241024

ACTIVE INGREDIENTS: CALCITRIOL 3 ug/1 g
INACTIVE INGREDIENTS: MINERAL OIL; .ALPHA.-TOCOPHEROL, DL-; PETROLATUM

HIGHLIGHTS OF PRESCRIBING INFORMATION

These highlights do not include all the information needed to use VECTICAL Ointment safely and effectively. See full prescribing information for VECTICAL Ointment.
VECTICAL Ointment, for topical use
Initial U.S. Approval: 1978

1 INDICATIONS AND USAGE

VECTICAL Ointment is a vitamin D analog indicated for the topical treatment of mild to moderate plaque psoriasis in adult and pediatric patients 2 years and older. (1.1)
Limitations of Use
The safety and effectiveness of VECTICAL Ointment in patients with known or suspected disorders of calcium metabolism have not been evaluated. (1.2)

RECENT MAJOR CHANGES

Indications and Usage (1) Date 07/2020
Dosage and Administration (2) Date 07/2020

2 DOSAGE AND ADMINISTRATION

Apply VECTICAL Ointment to affected areas of the body twice daily. (2)
Adults:
• The maximum weekly dose should not exceed 200 grams. (2)
Pediatrics:
• 2 to 6 years of age: the maximum weekly dose should not exceed 100 grams. (2)
• 7 years of age and older: the maximum weekly dose should not exceed 200 grams. (2)

For topical use only. (2)
Not for oral, ophthalmic, or intravaginal use. (2)

3 DOSAGE FORMS AND STRENGTHS

Ointment, 3 mcg/g (3)

4 CONTRAINDICATIONS

- None (4)

5 WARNINGS AND PRECAUTIONS

- Effects on Calcium metabolism: Risk of hypercalcemia. If aberrations in parameters of calcium metabolism are noted discontinue VECTICAL Ointment until these normalize. Increased absorption may occur with occlusive use. (5.1)
- VECTICAL Ointment should be used with caution in patients receiving medications known to increase the serum calcium level, such as thiazide diuretics, and in patients receiving calcium supplements or high doses of vitamin D. (5.1)

6 ADVERSE REACTIONS

Most common adverse reactions (incidence ≥ 3%) are hypercalcemia, hypercalciuria, and skin discomfort. (6.1)

To report SUSPECTED ADVERSE REACTIONS, contact: Galderma Laboratories, L.P. at 866-735-4137 or FDA at 1-800-FDA-1088 or www.fda.gov/medwatch .

FULL PRESCRIBING INFORMATION

1 INDICATIONS AND USAGE

1.1 Indication

VECTICAL Ointment is indicated for the topical treatment of mild to moderate plaque psoriasis in adults and pediatric patients 2 years and older.

1.2 Limitations of Use

The safety and effectiveness of VECTICAL Ointment in patients with known or suspected disorders of calcium metabolism have not been evaluated.

2 DOSAGE AND ADMINISTRATION

Apply VECTICAL Ointment to affected areas twice daily, morning and evening
Adults:
• The maximum weekly dose should not exceed 200 grams.
Pediatrics:
• 2 to 6 years of age: the maximum weekly dose should not exceed 100 grams
• 7 years of age and older: the maximum weekly dose should not exceed 200 grams
VECTICAL Ointment should not be applied to the eyes, lips, or facial skin.
VECTICAL Ointment is for topical use only.
VECTICAL Ointment is not for oral, ophthalmic or intravaginal use.

3 DOSAGE FORMS AND STRENGTHS

Ointment, 3 mcg/g. Each gram of VECTICAL Ointment contains 3 micrograms (mcg/g) of calcitriol.

4 CONTRAINDICATIONS

None

5 WARNINGS AND PRECAUTIONS

5.1 Effects on Calcium Metabolism

In controlled clinical trials hypercalcemia was observed in subjects exposed to VECTICAL Ointment. If aberrations in parameters of calcium metabolism occur, treatment should be discontinued until these parameters have normalized. The effects of VECTICAL Ointment on calcium metabolism following treatment durations greater than 52 weeks have not been evaluated. Increased absorption may occur with occlusive use. VECTICAL Ointment should be used with caution in patients receiving medications known to increase the serum calcium level, such as thiazide diuretics, and in patients receiving calcium supplements or high doses of vitamin D.

6 ADVERSE REACTIONS

6.1 Clinical Trials Experience

Because clinical studies are conducted under widely varying conditions, adverse reaction rates observed in the clinical studies of a drug cannot be directly compared to rates in the clinical studies of another drug and may not reflect the rates observed in practice.
VECTICAL Ointment was studied in two vehicle-controlled trials and one open label trial, resulting in 743 subjects exposed to VECTICAL Ointment. Table 1 describes adverse events in subjects treated with VECTICAL Ointment twice daily for 8 weeks. The population included subjects ages 13 to 87 years, males (284) and females (135), Caucasians (372) and non-Caucasians (47); with mild (105) to moderate (313) chronic plaque psoriasis.

Four hundred and nineteen subjects were treated with VECTICAL Ointment twice daily for 8 weeks. The population included subjects ages 13 to 87, males (284) and females (135), Caucasians (372) and non-Caucasians (47); with mild (105) to moderate (313) chronic plaque psoriasis.

Table 1. Selected Averse Events Occurring in at least 1% of Subjects in the Two Pooled Vehicle-Controlled Trials
 | VECTICAL (n = 419) | Vehicle Ointment (n = 420)
Discomfort skin | 3% | 2%
Pruritus | 1% | 1%

Among subjects having laboratory monitoring, hypercalcemia was observed in 24% (18/74) of subjects exposed to active drug and in 16% (13/79) of subjects exposed to vehicle, the elevations were less than 10% above the upper limit of normal) [see Warnings and Precautions (5.1) ].

The open label trial enrolled 324 subjects with psoriasis who were treated for up to 52 weeks and included 239 subjects exposed for 6 months and 116 subjects exposed for one year. Adverse events reported at a rate of greater than or equal to 3% of subjects treated with VECTICAL Ointment were lab test abnormality (8%), urine abnormality (4%), psoriasis (4%), hypercalciuria (3%), and discomfort of skin (3%). Kidney stones were reported in 3 subjects and confirmed in two.

6.2 Postmarketing Experience

The following adverse reactions have been identified during world-wide post-approval use of VECTICAL Ointment: acute blistering dermatitis, erythema and skin burning sensation. Because these reactions are reported voluntarily from a population of uncertain size, it is not always possible to reliably estimate their frequency or establish a causal relationship to drug exposure.

8 USE IN SPECIFIC POPULATIONS

8.1 Pregnancy

Risk Summary
Available data from pregnancies that occurred during the clinical development of VECTICAL Ointment and published case series of oral and intravenous calcitriol use in pregnant women have not identified a drug associated risk for major birth defects, miscarriages, or adverse maternal or fetal outcomes.
In animal reproduction studies, topical administration of calcitriol to pregnant rabbits during the period of organogenesis resulted in an increased incidence of fetal deaths, as well as an increased incidence of minor skeletal abnormalities (see Data). The available data do not allow the calculation of relevant comparisons between the systemic exposures of calcitriol observed in animal studies to the systemic exposures that would be expected in humans after topical use of VECTICAL Ointment.
The background risk of major birth defects and miscarriage for the indicated population is unknown. All pregnancies have a background risk of birth defect, loss, or other adverse outcomes. In the U.S. general population, the estimated risk of major birth defects and miscarriage in clinically recognized pregnancies is 2 to 4% and 15 to 20%, respectively.

Data
Animal Data
Embryo-fetal development studies with calcitriol were performed in which rats were treated orally at dosages up to 0.9 mcg/kg/day (5.4 mcg/m^2/day) and in which rabbits received topical application of calcitriol ointment (3 ppm) to 6.4% of the body surface area. No effects on reproductive or fetal parameters were observed in rats. In rabbits, topically applied calcitriol induced a significantly elevated mean post-implantation loss and an increased incidence of minor skeletal abnormalities due to delayed ossification of the pubic bones. A slightly increased incidence of skeletal variation (extra 13th rib, reduced ossification of epiphyses) was also observed. These effects may have been secondary to maternal toxicity.

8.2 Lactation

Risk Summary
There are no data on the presence of calcitriol in human milk, the effects on the breastfed infant or on milk production after treatment with VECTICAL Ointment. It is not known whether topical administration of calcitriol could result in sufficient systemic absorption to produce detectable quantities in human milk. The developmental and health benefits of breastfeeding should be considered along with the mother’s clinical need for VECTICAL Ointment and any potential adverse effects on the breastfed infant from VECTICAL Ointment or from the underlying maternal conditions.
Clinical Considerations
Advise breastfeeding women not to apply VECTICAL Ointment directly to the nipple and areola to avoid direct infant exposure.

8.4 Pediatric Use

The safety and effectiveness of VECTICAL Ointment have been established in pediatric patients age 2 years and older for topical treatment of mild to moderate psoriasis. Use of VECTICAL Ointment in this age group is supported by two adequate and well-controlled 8-week trials and an open label trial in adult subjects, and additional data from trials conducted in pediatric subjects 2 to 17 years of age including;

- a vehicle controlled 8-week trial in 19 subjects 2 to 12 years of age with mild to moderate plaque psoriasis
- an open-label 8-week safety and pharmacokinetics (PK) trial in 25 subjects 12 to 17 years of age
- an open-label 14-day safety and PK trial in 18 subjects 2 to 12 years of age; and
- an open-label 26-week safety and PK trial in 54 subjects 2 to 17 years of age.

Data from 63 subjects ages 2 to 12 years, and 42 subjects ages 13 to 17 years showed no significant effects on indices of calcium metabolism. The systemic exposure of calcitriol in the pediatric subjects was generally comparable to the endogenous levels observed at baseline. No new safety signals were identified in subjects 2 to 17 years [see Clinical Studies (14), Clinical Pharmacology (12.3) and Adverse Reactions (6.1)].
The safety and effectiveness of VECTICAL Ointment in pediatric subjects below the age of 2 years have not been established.

8.5 Geriatric Use

Clinical studies of VECTICAL Ointment did not include sufficient numbers of subjects aged 65 and over to determine whether they respond differently from younger subjects. Other reported experience has not identified differences in responses between the elderly and younger patients.

10 OVERDOSAGE

Topically applied calcitriol can be absorbed in sufficient amounts to produce systemic effects [ see Warningsand Precautions (5.1) ].

11 DESCRIPTION

VECTICAL (calcitriol) Ointment 3 mcg/g is a vitamin D analog intended for topical application to the skin. The chemical name of the active ingredient is (5Z,7E)-9,10-secocholesta-5,7,10(19)-triene-1α,3β,25-triol. The structural formula is:

Calcitriol is a white or almost white crystalline solid. It is practically insoluble in water, soluble in alcohol and in fatty oils. The molecular formula is C27H44O3, and the molecular weight is 416.64.

VECTICAL Ointment is a translucent ointment containing 3 mcg/g (0.0003% w/w) of calcitriol, packaged in aluminum tubes with screw caps. Other components of the ointment are mineral oil, dl-α-tocopherol, and white petrolatum.

12 CLINICAL PHARMACOLOGY

The contribution to efficacy of individual components of the vehicle has not been established.

12.1 Mechanism of Action

The mechanism of action of calcitriol in the treatment of psoriasis has not been established.

12.3 Pharmacokinetics

The systemic exposure of calcitriol was assessed in subjects with chronic, plaque psoriasis. In the pivotal pharmacokinetic/pharmacodynamic study, calcitriol ointment 3 mcg/g, was applied twice daily for 21 days (for a total dose of 30 g/day) to 35% of the body surface area (psoriatic + surrounding healthy skin) of subjects with at least 25% of body surface area involvement. At Day 21, the geometric mean plasma concentration values of Cmaxincreased by approximately 36% over baseline and the geometric mean value of AUC(0 – 12 hr)increased by 44%. There was no correlation between the elevated calcitriol levels and the pharmacodynamic parameters of serum albumin adjusted calcium, serum phosphorus, urinary calcium and urinary phosphorus.

Specific Populations
Pediatric Patients
The systemic exposure of calcitriol was assessed in pediatric subjects ages 2 to 17 years with plaque psoriasis in two trials. In one trial, 25 subjects ages 12 to 17 applied calcitriol ointment 3 mcg/g twice a day for 8 weeks to a body surface area of 10% to 35%. The mean daily dose was 10.43 g/day. In the second trial, 17 subjects ages 2 to 12 applied calcitriol ointment 3 mcg/g twice a day for 14 days to a body surface area of 3% to 18%. The mean daily dose was 17.09 g/day. In both trials, the systemic concentrations of calcitriol post treatment were relatively flat and were generally comparable to the endogenous levels observed at baseline. The PK parameters could not be reliably estimated.
There was no correlation between the elevated calcitriol levels and the pharmacodynamic parameters of serum albumin adjusted calcium, serum phosphorus, urinary calcium and urinary phosphorus.

13 NONCLINICAL TOXICOLOGY

13.1 Carcinogenesis, Mutagenesis, Impairment of Fertility

When calcitriol was applied topically to mice for up to 24 months, no significant changes in tumor incidence were observed. Concentrations of calcitriol in ointment base of 0 (vehicle control), 0.3, 0.6 and 1.0 ppm were evaluated.

A two-year carcinogenicity study was conducted in which calcitriol was orally administered to rats at dosages of approximately 0.005, 0.03, and 0.1 mcg/kg/day (0.03, 0.18, and 0.6 mcg/m^2/day, respectively). The incidence of benign pheochromocytomas was significantly increased in female rats. No other significant differences in tumor incidence were observed.

Calcitriol did not elicit genotoxic effects in the mouse lymphoma TK locus assay. Studies in which male and female rats received oral doses of calcitriol of up to 0.6 mcg/kg/day (3.6 mcg/m^2/day) indicated no impairment of fertility or general reproductive performance.

14 CLINICAL STUDIES

In two, multicenter, double-blind, vehicle-controlled studies, a total of 839 subjects with psoriasis rated "mild" or "moderate" using an investigator global assessment scale were treated twice daily for 8 weeks. Subjects were randomized in a 1:1 ratio to receive either VECTICAL Ointment or vehicle ointment. The mean age of the subjects was 48 years and 66% were male; most subjects were rated "moderate" at baseline.

Success was defined as "Clear or Minimal" (up to light red or pink in coloration, surface dryness with some white coloration, and slight elevation above normal skin) with at least a 2-grade change from baseline. The success rates are displayed in the Table 2.

Table 2. Percentage of Subjects with Clear or Minimal Disease AND Two Grade Improvement at End of Treatment (8 weeks)
Study 1 |  | Study 2
VECTICAL Ointment (N = 209) | Vehicle Ointment (N = 209) | VECTICAL Ointment (N = 210) | Vehicle Ointment (N = 211)
23.4% | 14.4% | 20.5% | 6.6%

16 HOW SUPPLIED/STORAGE AND HANDLING

16.1 How Supplied

VECTICAL Ointment 3 mcg/g is available in collapsible aluminum tubes of the following package sizes:

- 100 g tube (NDC 0299-2012-10)

16.2 Storage

Store at Controlled Room temperature 68° - 77°F (20° - 25°C) with excursions permitted between 59° - 86°F (15° - 30°C). [See USP Controlled Room Temperature.] Do not freeze or refrigerate.

17 PATIENT COUNSELING INFORMATION

Advise the patient to read the FDA-approved patient labeling (Patient Information).

Patients using VECTICAL Ointment should receive the following information:

- This medication is to be used as directed by the physician. It is for external use only. This medication is to be applied only to areas of the skin affected by psoriasis, as directed. It should be gently rubbed into the skin so that no medication remains visible.
- This medication may affect calcium metabolism. Hypercalcemia has been observed in subjects exposed to this medicine. Increased absorption may occur with use of occlusive dressings.
- Avoid use of more than 100 grams per week in patients ages 2-6 years and use of more than 200 grams per week in patients ages 7 years and older.
- Instruct patients to report any signs of adverse reactions to their physician.
- Avoid contact with eyes, lips, and facial skin.
- Advise breastfeeding women not to apply VECTICAL Ointment directly to the nipple and areola to avoid direct infant exposure [see Use in Specific Populations (8.2)].

To report SUSPECTED ADVERSE REACTIONS, contact Galderma Laboratories, L.P. at 866-735-4137 or FDA at 1-800-FDA-1088 or www.fda.gov/medwatch.

US Patent No. 7,749,986
Marketed by:
GALDERMA LABORATORIES, L.P.
Dallas, Texas 75201 USA
Made in Canada.
Galderma is a registered trademark.
P51460-6

PATIENT INFORMATION
VECTICAL® (Vek te kal)
(calcitriol) Ointment

Important: VECTICAL Ointment is for use on the skin only (topical use).Do not use VECTICAL Ointment in your mouth, eyes, or vagina.
What is VECTICAL Ointment?
VECTICAL Ointment is a prescription medicine used on the skin (topical) to treat mild to moderate plaque psoriasis in adults and children 2 years and older.
It is not known if VECTICAL Ointment is safe and effective in children under 2 years of age.
It is not known if VECTICAL Ointment is safe and effective in people with known or suspected problems with calcium metabolism.

Before using VECTICAL Ointment, tell your healthcare provider about all your medical conditions, including if you:

- are pregnant or planning to become pregnant. It is not known if VECTICAL Ointment will harm your unborn baby.
- are breastfeeding or plan to breastfeed. It is not known if VECTICAL Ointment passes into your breast milk. Talk to your healthcare provider about the best way to feed your baby during treatment with VECTICAL Ointment.
  - If you use VECTICAL Ointment and breastfeed, do not apply VECTICAL Ointment to your nipple and areola to avoid getting VECTICAL Ointment into your baby’s mouth.

Tell your healthcare provider about all of the medicines you take, including prescription and over-the-counter medicines, vitamins, and herbal supplements.
Especially tell your healthcare provider if you take:

- medicines that can increase your calcium levels, such as water pills (thiazide diuretics)
- calcium or vitamin D supplements

Ask your healthcare provider or pharmacist for a list of these medicines if you are not sure if you are taking any of the medicines listed above.
Know the medicines you take. Keep a list of them to show your healthcare provider and pharmacist when you get a new medicine.

How should I use VECTICAL Ointment?

- Use VECTICAL Ointment exactly as your healthcare provider tells you to use it.
- Apply VECTICAL Ointment to the affected areas 2 times each day in the morning and evening.
- Adults and children 7 years of age and older should not use more than 200 grams in 1 week.
- Children 2 to 6 years of age should not use more than 100 grams in 1 week.
- Avoid applying VECTICAL Ointment to your eyes, lips, or facial skin.
- Apply only enough VECTICAL Ointment to cover your affected skin area.
- You should not cover the treated area(s) with a waterproof (occlusive) bandage or overdosage may occur.
- Gently rub VECTICAL Ointment into the affected area until it disappears into your skin.
- Wash your hands after using VECTICAL Ointment, unless you are using the medicine to treat your hands.

What are the possible side effects of VECTICAL Ointment?
VECTICAL Ointment may cause serious side effects, including:

- Too much calcium in your blood (hypercalcemia) may occur with VECTICAL Ointment.Your healthcare provider may tell you to stop using VECTICAL Ointment until your calcium levels become normal.
- The most common side effects of VECTICAL Ointment includeincreased urine calcium level, itching, and skin discomfort.

These are not all of the possible side effects of VECTICAL Ointment.
Call your doctor for medical advice about side effects. You may report side effects to FDA at 1-800-FDA-1088.
You may also report side effects to Galderma Laboratories, L.P. at 1-866-735-4137.

How should I store VECTICAL Ointment?

- Store VECTICAL Ointment at room temperature between 68°F to 77°F (20°C to 25°C).
- Do not freeze or refrigerate VECTICAL Ointment.

Keep VECTICAL Ointment and all medicines out of the reach of children.

General information about the safe and effective use of VECTICAL Ointment.
Medicines are sometimes prescribed for purposes other than those listed in a Patient Information leaflet. Do not use VECTICAL Ointment for a condition for which it was not prescribed. Do not give VECTICAL Ointment to other people, even if they have the same symptoms that you have. It may harm them. You can ask your healthcare provider or pharmacist for information about VECTICAL Ointment that is written for health professionals.

What are the ingredients in VECTICAL Ointment?
Active ingredient:calcitriol
Inactive ingredients:mineral oil, dl-α-tocopherol, and white petrolatum.

Manufactured by:

G. Production Inc.

Baie d’Urfé, QC H9X 3S4 Canada

This Patient Information has been approved by the U.S. Food and Drug Administration
Revised: 10/2022

PACKAGE LABEL - 100 g CARTON

Vectical®
(calcitriol) Ointment 3 mcg/g
FOR TOPICAL USE ONLY
NDC 0299-2012-10
Rx Only
NET WT. 100 g
GALDERMA

For topical use only. Not for ophthalmic, oral or intravaginal use.
Usual dosage: Apply to affected areas twice daily. See package insert for complete prescribing information.
Each gram contains:calcitriol 3mcg in an ointment base consisting of mineral oil, dl-α-tocopherol, and white petrolatum,

Storage:Store at controlled room temperature 68° - 77° (20° -25°C) with excursions permitted between 59° - 86°F (15° - 30°C).
Do not freeze or refrigerate.
Marketed by: GALDERMA LABORATORIES, L.P.
Dallas, Texas 75201 USA
Made in Canada.
All trademarks are the property of their respective owners.
P51459-6